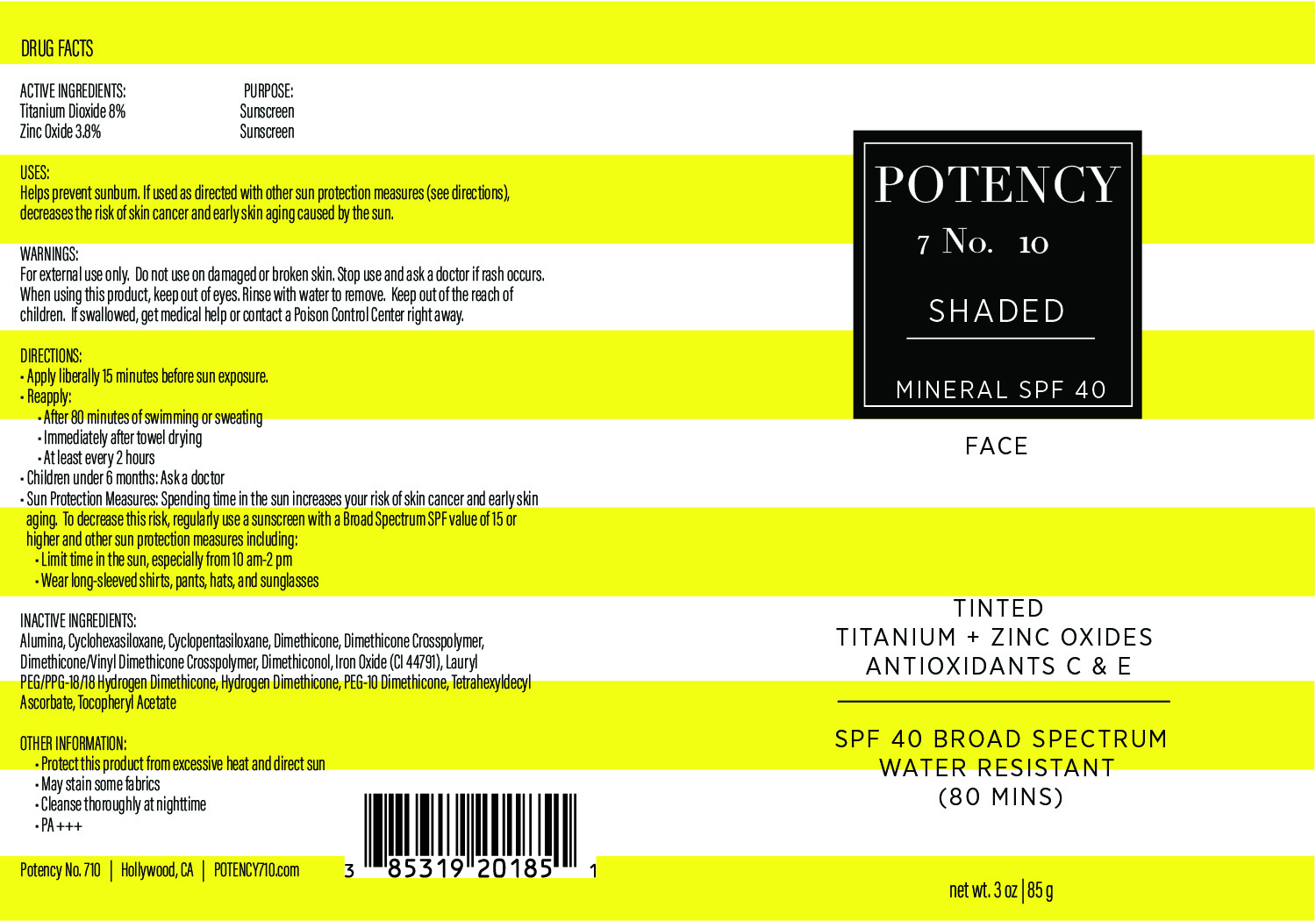 DRUG LABEL: SHADED
NDC: 85319-201 | Form: CREAM
Manufacturer: Potency No. 710 LLC
Category: otc | Type: HUMAN OTC DRUG LABEL
Date: 20251210

ACTIVE INGREDIENTS: TITANIUM DIOXIDE 80 mg/1 g; ZINC OXIDE 38 mg/1 g
INACTIVE INGREDIENTS: CYCLOHEXASILOXANE; ALUMINA; CYCLOPENTASILOXANE; DIMETHICONE; DIMETHICONE/VINYL DIMETHICONE CROSSPOLYMER (SOFT PARTICLE); DIMETHICONOL (2000 CST); CI 77491; CI 77492; PEG-10 DIMETHICONE (600 CST); LAURYL PEG/PPG-18/18 METHICONE; ALPHA-TOCOPHEROL ACETATE; DIMETHICONE CROSSPOLYMER; TETRAHEXYLDECYL ASCORBATE; CI 77499; HYDROGEN DIMETHICONE (20 CST)

Active Ingredients:

Titanium Dioxide 8% Zinc Oxide 3.8%

Purpose:

Sunscreen

Uses:

Helps prevents sunburn. If used as directed with other sun protection measures (see Directions), decreases the risk of skin cancer and early skin aging caused by the sun.

Warnings:

For external use only. Do not use on damaged or broken skin. Stop use and ask a doctor if rash occurs. When using this product, keep out of eyes. Rinse with water to remove. Keep out of the reach of children. If swallowed, get medical help or contact a poison control center right away.

Warnings:

Keep out of the reach of children

Directions:

• Apply liberally 15 minutes before sun exposure. • Reapply: • After 80 minutes of swimming or sweating • Immediately after towel drying • At least every 2 hours • Children under 6 months: Ask a doctor • Sun Protection Measures: Spending time in the sun increases your risk of skin cancer and early skin aging. To decrease this risk, regularly use a sunscreen with a Broad Spectrum SPF value of 15 or higher and other sun protection measures including: •Limit time in the sun, especially from 10 am-2 pm •Wear long-sleeved shirts, pants, hats, and sunglasses

Inactive Ingredietns:

Alumina, Cyclohexasiloxane, Cyclopentasiloxane, Dimethicone, Dimethicone Crosspolymer, Dimethicone/Vinyl Dimethicone Crosspolymer, Dimethiconol, Iron Oxide (CI 77491), Lauryl PEG/PPG-18/18 Methicone, Hydrogen Dimethicone, PEG-10 Dimethicone, Tetrahexyldecyl Ascorbate, Tocopheryl Acetate

Other Information:

- Protect this product from excessive heat and direct sun.
- May stain some fabrics.
- Cleanse thoroughly at nighttime.
- PA +++